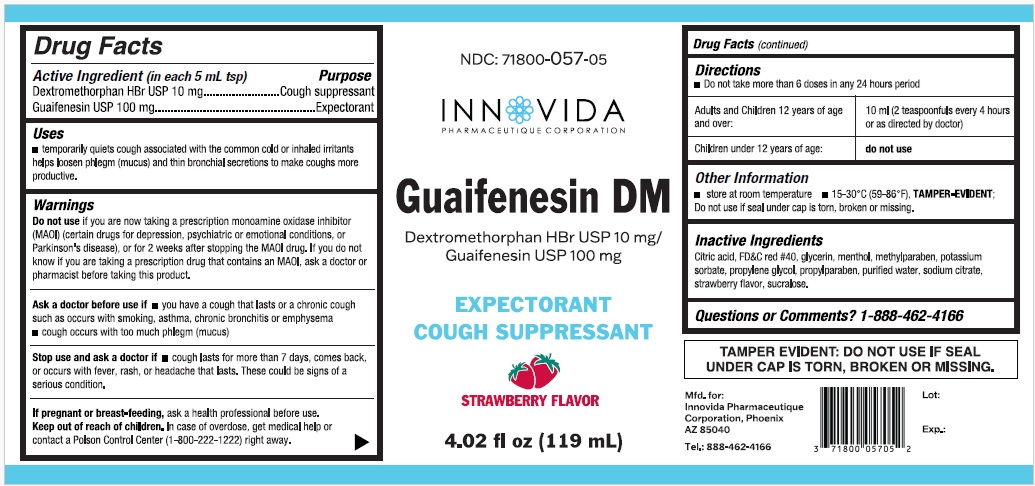 DRUG LABEL: Guaifenesin DM
NDC: 71800-057 | Form: LIQUID
Manufacturer: Innovida Pharmaeutique Corporation
Category: otc | Type: HUMAN OTC DRUG LABEL
Date: 20250325

ACTIVE INGREDIENTS: DEXTROMETHORPHAN HYDROBROMIDE 10 mg/5 mL; GUAIFENESIN 100 mg/5 mL
INACTIVE INGREDIENTS: CITRIC ACID; FD&C RED NO. 40; GLYCERIN; MENTHOL; METHYLPARABEN; POTASSIUM SORBATE; PROPYLENE GLYCOL; PROPYLPARABEN; WATER; SODIUM CITRATE; SUCRALOSE; STRAWBERRY

Active Ingredient (in each 5mL tsp)

Dextromethorphan HBr. USP 10 mg
Guaifenesin USP 100 mg

Purpose

Cough Suppressant
Expectorant

Uses

- temporarily relieves cough due to minor throat and bronchial irritation as may occur with a cold
- helps loosen phlegm (mucus) and thin bronchial secretions to drain bronchial tubes

Warnings

Do not useif you are now taking a prescription monoamine oxidase inhibitor (MAOI) (certain drugs for depression, psychiatric, or emotional conditions, or Parkinson’s disease) or for 2 weeks after stopping the MAOI drug. If you do not know if your prescription drug contains an MAOI, ask a doctor or pharmacist before taking this product.

Ask a doctor before use if you have
• cough that occurs with too much phlegm (mucus)
• cough that lasts or is chronic such as occurs with smoking, asthma, chronic bronchitis, or emphysema

Stop use and ask a doctor ifcough lasts more than 7 days, comes back, or is accompanied by fever, rash, or persistent headache. These could be signs of a serious condition.

If pregnant or breast-feeding, ask a healthcare professional before use.
Keep out of reach of children. In case of accidental overdose, get medical help or contact a Poison Control Center right away. (1-800-222-1222)

Directions

do not take more than 6 doses in any 24 hour period

Adults and Children 12 years of age and over | 10mL (2 teaspoonfuls every 4 hours or as directed by doctor)
Children under 12 years of age | Do not use

Other Information

- store at room temperature
- 15° to 30°C (59° to 86°F) TAMPER-EVIDENT;
- do not use if seal under cap is torn broken or missing.

Inactive Ingredients

CITRIC ACID, FD&C RED NO. 40, GLYCERIN, GLYCERIN, METHYLPARABEN, POTASSIUM SORBATE, PROPYLENE GLYCOL, PROPYLPARABEN, WATER, SODIUM CITRATE, Strawberry Flavor, SUCRALOSE